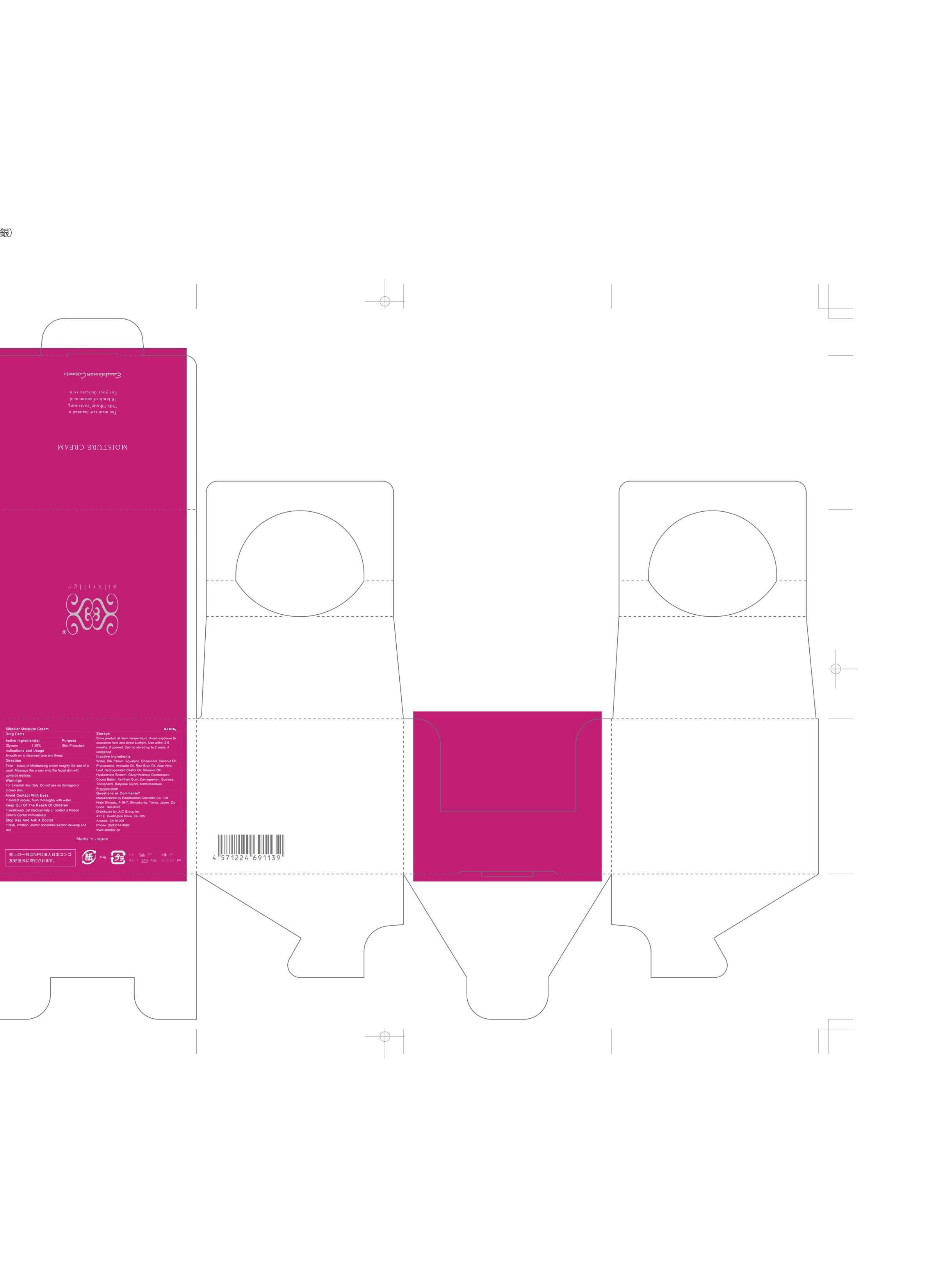 DRUG LABEL: Moisture Cream
NDC: 69893-201 | Form: CREAM
Manufacturer: Eaudeleman Cosmetic Co Ltd
Category: otc | Type: HUMAN OTC DRUG LABEL
Date: 20151104

ACTIVE INGREDIENTS: GLYCERIN 4.2 g/100 g
INACTIVE INGREDIENTS: WATER; SILK FIBROIN; SQUALANE; DOCOSANOL; COCONUT OIL; PROPANEDIOL; AVOCADO OIL; RICE BRAN OIL; ALOE VERA LEAF; HYDROGENATED CASTOR OIL; SHEANUT OIL; HYALURONATE SODIUM; GLYCYRRHIZINATE DIPOTASSIUM; COCOA BUTTER; XANTHAN GUM; CARRAGEENAN; SUCROSE; TOCOPHEROL; BUTYLENE GLYCOL; METHYLPARABEN; PROPYLPARABEN

Eaudeleman Cosmetic

Active Ingredient

Glycerin 4.20%

Purpose

Glycerin Skin Protectant

Indications and Usage

Smooth on to cleansed face and throat.

Directions

Take 1 scoop of moisturizing cream roughly the size of a pearl. Massage the cream into facial skin with upwards motions.

Warnings

For external use only. Do not use on damaged or broken skin.

Keep Out of Reach of Children.

If swallowed, get medical help or contact a Poison Control Center immediately.

Avoid Contact With Eyes.

If contact occurs, flush thoroughly with water.

Stop Use and Ask a Doctor If

Rash, irritation and/or abnormal reaction develop and last.

Storage

Store product at room temperature. Avoid exposure to excessive heat and direct sunlight. Use with 3-6 months if opened. Can be stored up to 2 years if not opened.

Questions or Comments?

Manufactured by Eaudeleman Cosmetic Co.; Ltd
Nishi Shinjuku 7-16-7, Shijuku-ku, Tokyo, Japan 160-0023

Distributed by JUC Group Inc.
411 E. Huntington Drive, Suite 205
Arcadia, CA 91006
Phone: (626)574-8588

www.silkriller.com

Inactive Ingredients

WATER, SILK FIBROIN, SQUALANE, DOCOSANOL, COCONUT OIL, PROPANEDIOL, AVOCADO OIL, RICE BRAN OIL, ALOE VERA LEAF, HYDROGENATED CASTOR OIL, SHEANUT OIL, HYALURONATE SODIUM, GLYCYRRHIZINATE DIPOTASSIUM, COCOA BUTTER, XANTHAN GUM, CARRAGEENAN, SUCROSE, TOCOPHEROL, BUTYLENE GLYCOL, METHYLPARABEN, PROPYLPARABEN